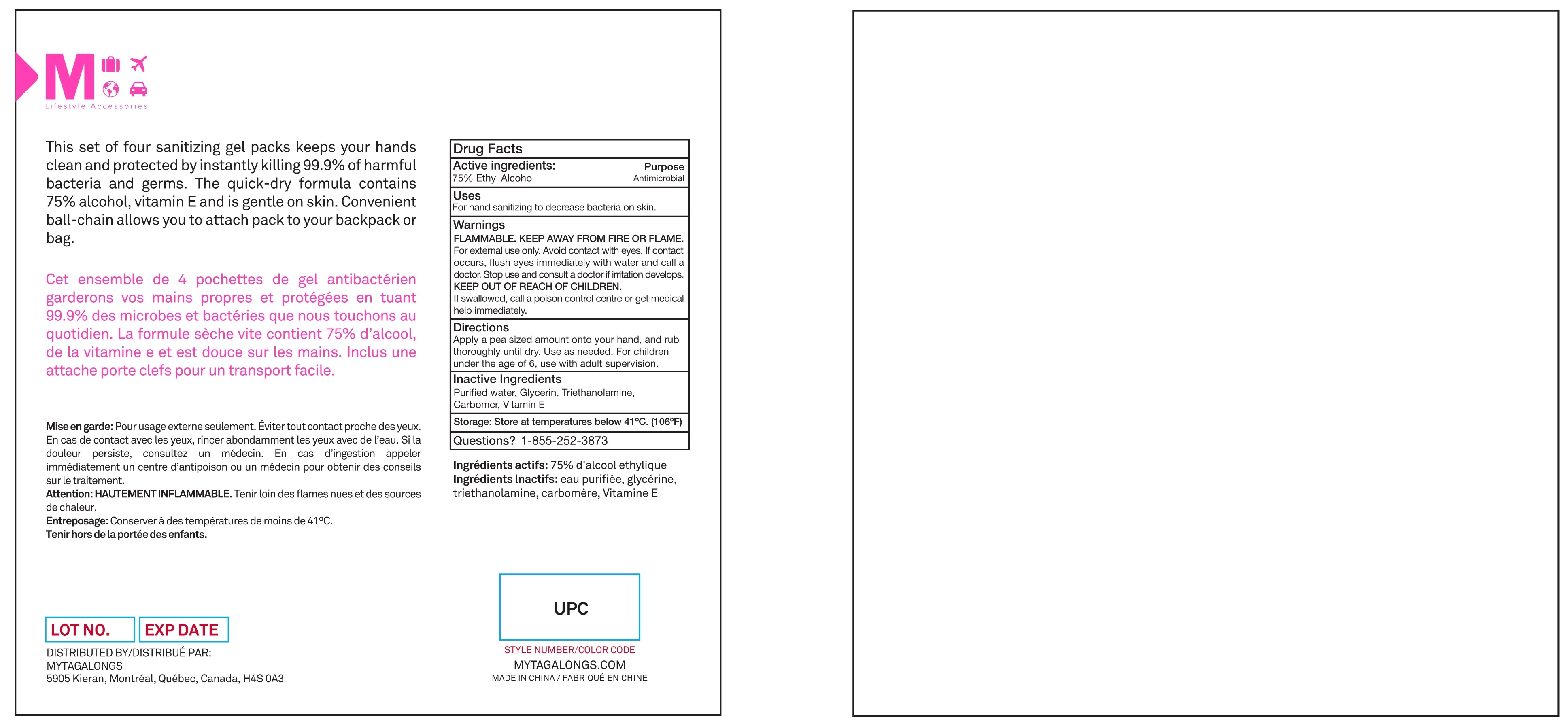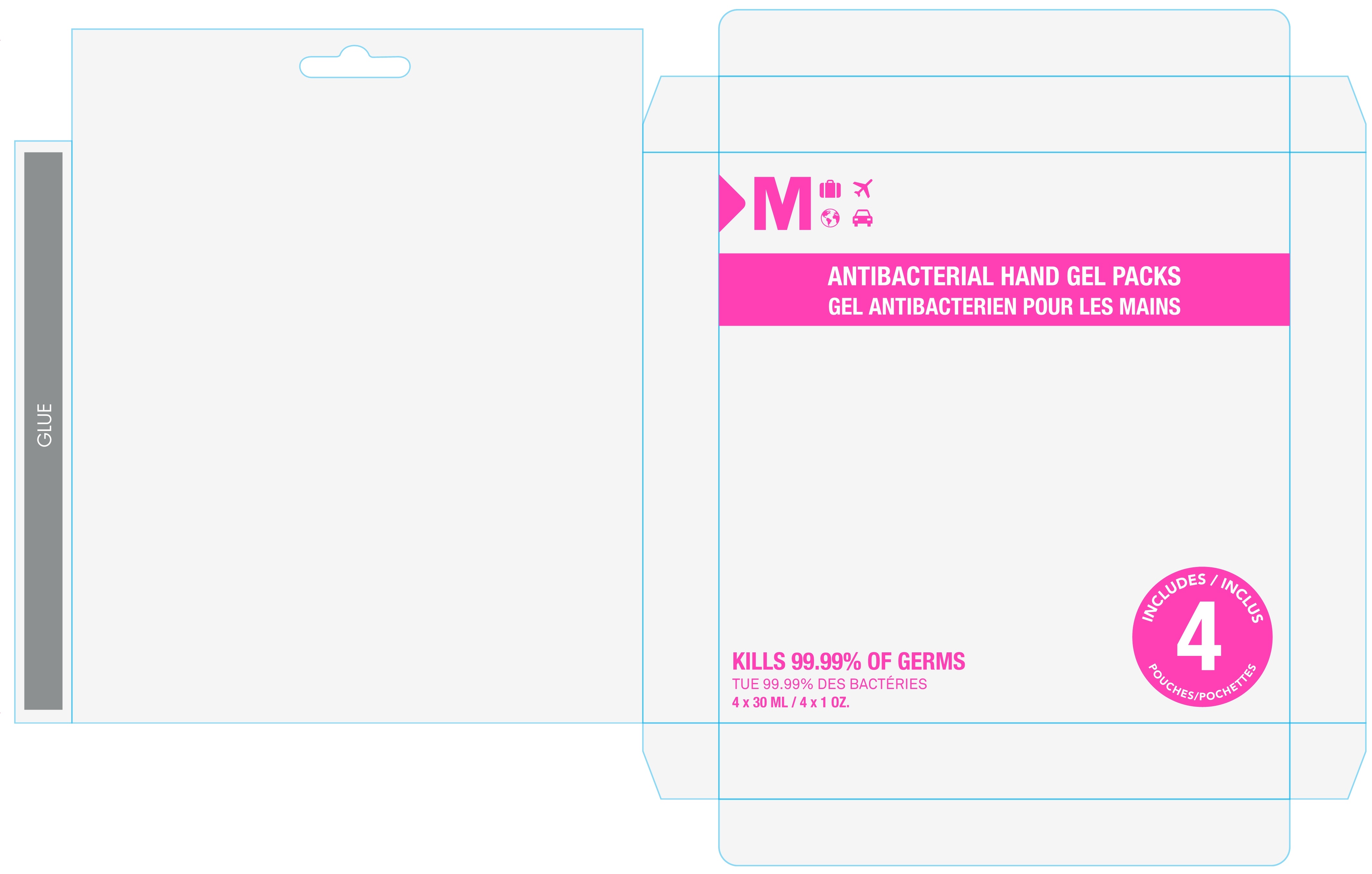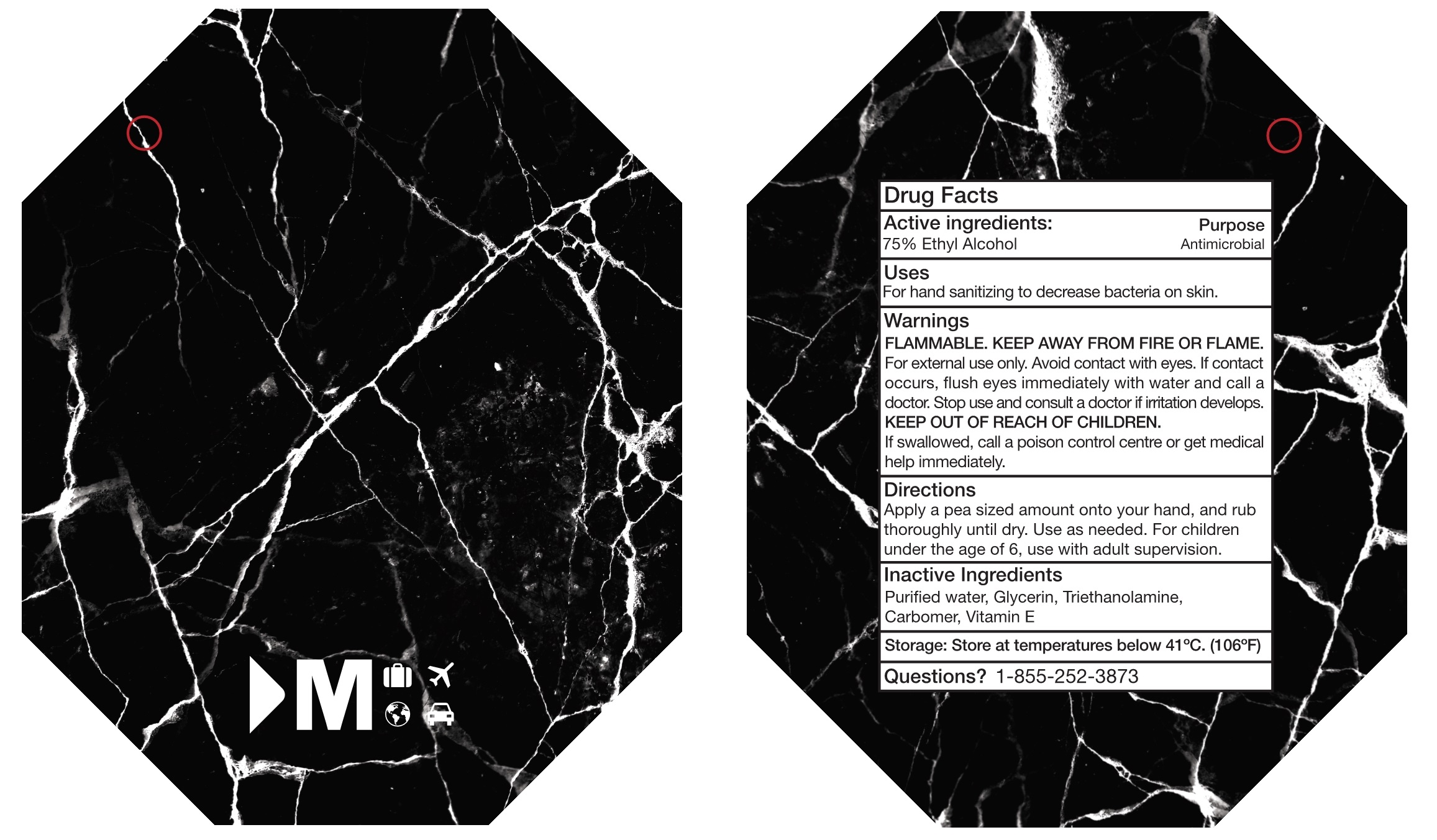 DRUG LABEL: 75% HAND SANITIZER
NDC: 74763-019 | Form: GEL, METERED
Manufacturer: Zhejiang Gafle Auto Chemical Co., Ltd.
Category: otc | Type: HUMAN OTC DRUG LABEL
Date: 20220328

ACTIVE INGREDIENTS: ALCOHOL 75 mL/100 mL
INACTIVE INGREDIENTS: CARBOMER 940; .ALPHA.-TOCOPHEROL; WATER; TROLAMINE; GLYCERIN

74763-019
75% HAND SANITIZER

ACTIVE INGERDIENT

75%Ethyl Alcohol

PURPOSE

Antimicrobial

USES

For hand sanitizing to decrease bacteria on skin.

WARNINGS

FLAMMABLE.KEEP AWAY FROM FIRE OR FLAME.
For external use only.Avoid contact with eyes.If contact occurs， flush eyes immediately with water and call a doctor.

DO NOT USE

/

Stop use and consulta doctor ii rita tion develops.

KEEP OUT OF REACH OF CHILDREN.
If swallowed， call a poison control centre or get medical help immediately.

Stop use and consulta doctor ii rita tion develops.

KEEP OUT OF REACH OF CHILDREN

If swallowed， call a poison control centre or get medical help immediately.

DIRECTIONS

Apply ape a sized amount on to your hand， and rub thoroughly until dry.Use as needed.For children under the age of 6， use with adult supervision.

OTHER INFORMATION

Storeattemperaturesbelow41℃.(106°F)

INACTIVE INGERDIENTS

Purified water， Glycerin， Triethanolamine， Carbomer， VitaminE

Package Label - Principal Display Panel

74763-019-01 Front of outer packaging

74763-019-01 Back of outer packaging

74763-019-11 inner packaging